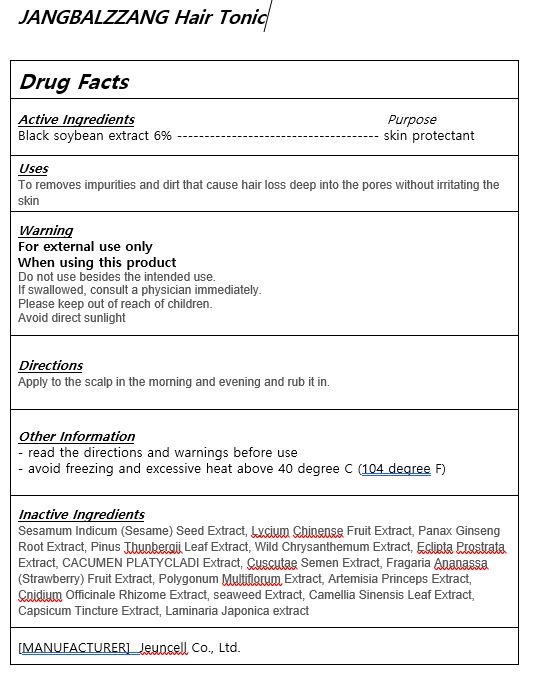 DRUG LABEL: JANGBALZZANG HAIR TONIC
NDC: 54296-0005 | Form: LIQUID
Manufacturer: Jeuncell Co.,Ltd
Category: otc | Type: HUMAN OTC DRUG LABEL
Date: 20230922

ACTIVE INGREDIENTS: SOYBEAN OIL 6 g/100 mL
INACTIVE INGREDIENTS: WATER; PINUS THUNBERGII LEAF

ACTIVE INGREDIENT

black soybean extracts

INACTIVE INGREDIENT

Sesamum Indicum (Sesame) Seed Extract, Lycium Chinense Fruit Extract, Panax Ginseng Root Extract, Pinus Thunbergii Leaf Extract, Wild Chrysanthemum Extract, Eclipta Prostrata Extract, CACUMEN PLATYCLADI Extract, Cuscutae Semen Extract, Fragaria Ananassa (Strawberry) Fruit Extract, Polygonum Multiflorum Extract, Artemisia Princeps Extract, Cnidium Officinale Rhizome Extract, seaweed Extract, Camellia Sinensis Leaf Extract, Capsicum Tincture Extract, Laminaria Japonica extract

PURPOSE

to clean scalp and norishment

Do not use besides the intended use.
If swallowed, consult a physician immediately.
Please keep out of reach of children.
Avoid direct sunlight

KEEP OUT OF REACH OF CHILDREN

Please keep out of reach of children.

Uses

Apply to the scalp in the morning and evening and rub it in.

DOSAGE AND ADMINISTRATION

for external use only